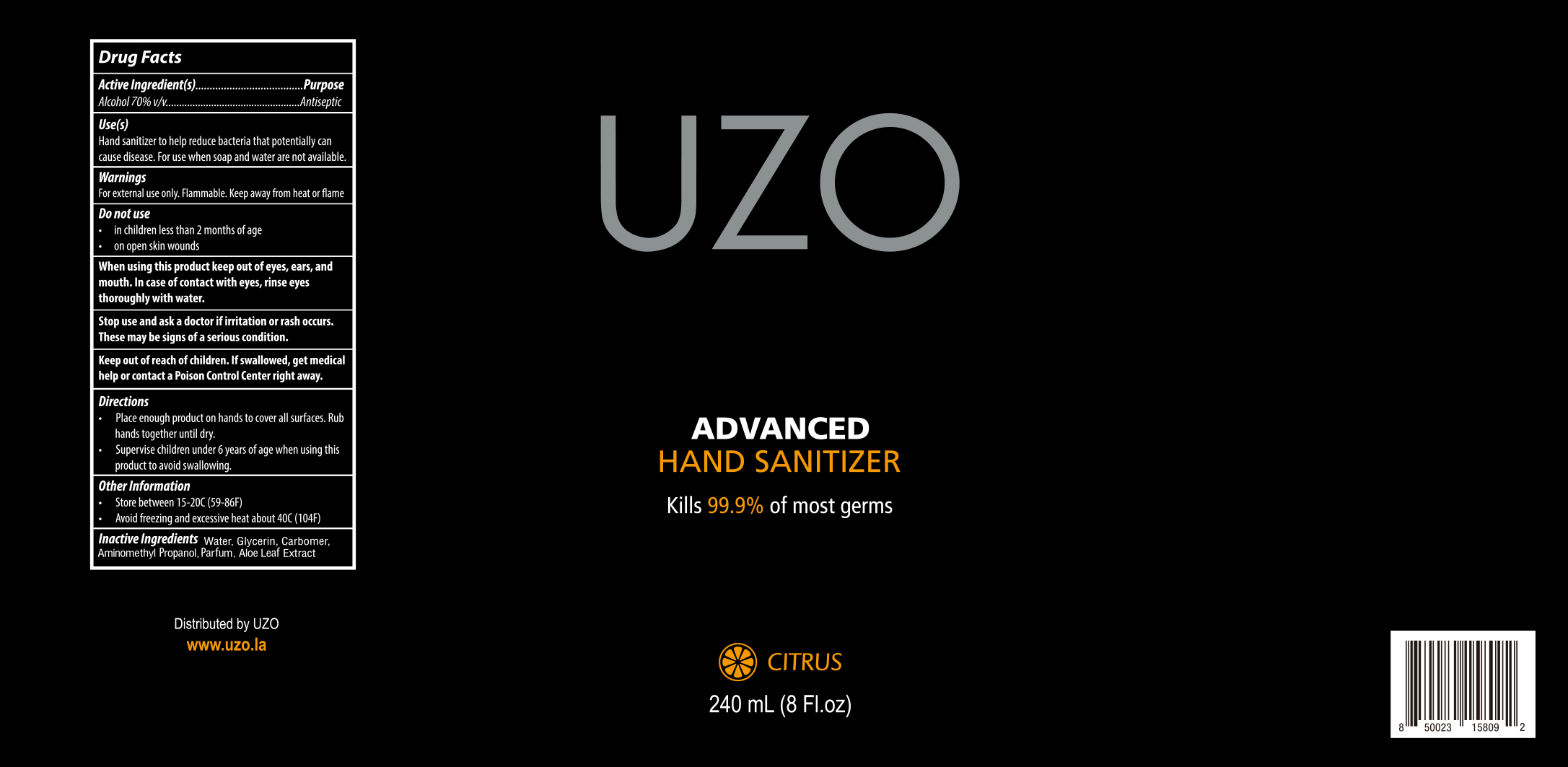 DRUG LABEL: UZO Hand Sanitizer
NDC: 79740-005 | Form: LIQUID
Manufacturer: ANTHOS GROUP, INC, THE
Category: otc | Type: HUMAN OTC DRUG LABEL
Date: 20240220

ACTIVE INGREDIENTS: ALCOHOL 70 mL/100 mL
INACTIVE INGREDIENTS: CARBOMER HOMOPOLYMER, UNSPECIFIED TYPE; GLYCERIN; WATER; ALOE VERA LEAF; METHYL BENZOATE; AMINOMETHYLPROPANOL

79740-005 信息更新
UZO Hand Sanitizer

Active Ingredient(s)

Alcohol 70% v/v

Purpose

Antiseptic

Use

Hand sanitizer to help reduce bacteria that potentiaily can cause disease. for use when soap and water are not available.

Warnings

For external use only. Flammable. Keep away from heat or flame

Do not use
in children less than 2 months of age
on open skin wounds

When using this product keep out of eyes, ears, and mouth. In case of contact with eyes, rinse eyes thoroughly with water.

Stop use and ask a doctor if irritation or rash occurs.
These may be signs of a serious condition.

Keep out of reach of children. If swallowed, get medical help or contact a Poison Control Center right away.

Do not use

in children less than 2 months of age
on open skin wounds

Stop use and ask a doctor if irritation or rash occurs.
These may be signs of a serious condition.

When using this product keep out of eyes, ears, and mouth. In case of contact with eyes, rinse eyes thoroughly with water.

Stop use and ask a doctor if irritation or rash occurs.
These may be signs of a serious condition.

Keep out of reach of children. If swallowed, get medical help or contact a Poison Control Center right away.

Keep out of reach of children. If swallowed, get medical help or contact a Poison Control Center right away.

Directions

Place enough Product on hands to cover all surfaces. Rub hands together until dry.
Supervise children under 6 years of age when using this product to avoid swallowing.

Other information

Store between 15-20C(59-86F)
Avoid freezing and excessive heat about 40C(104F)

Inactive ingredients

water, Glycerin, Carbomer, Aminomethyl Propanol, Parfum, Aloe Leaf Extract